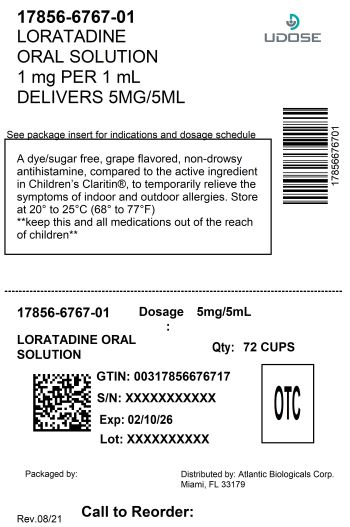 DRUG LABEL: Childrens Loratadine Oral
NDC: 17856-6767 | Form: SOLUTION
Manufacturer: Atlantic Biologicals
Category: otc | Type: HUMAN OTC DRUG LABEL
Date: 20260205

ACTIVE INGREDIENTS: LORATADINE 5 mg/5 mL
INACTIVE INGREDIENTS: EDETATE DISODIUM; GLYCERIN; MALTITOL; SODIUM PHOSPHATE, MONOBASIC, UNSPECIFIED FORM; PHOSPHORIC ACID; PROPYLENE GLYCOL; WATER; SODIUM BENZOATE; SORBITOL; SUCRALOSE

Children’s Loratadine Oral Solution Drug Facts

Active ingredient (in each 5 mL teaspoonful)

Loratadine 5 mg

Purpose

Antihistamine

Uses

temporarily relieves these symptoms due to hay fever or other upper respiratory allergies:

- runny nose
- itchy, watery eyes
- sneezing
- itching of the nose or throat

Warnings

Do not use

if you have ever had an allergic reaction to this product or any of its ingredients

Ask a doctor before use if you have

liver or kidney disease. Your doctor should determine if you need a different dose.

When using this product

do not take more than directed. Taking more than directed may cause drowsiness.

Stop use and ask a doctor if

an allergic reaction to this product occurs. Seek medical help right away.

If pregnant or breast feeding,

ask a health professional before use.

Keep out of reach of children.

In case of overdose, get medical help or contact a Poison Control Center right away (1-800-222-1222).

Directions

- use only with enclosed dosing cup

adults and children 6 years and over | 2 teaspoonfuls (tsp) daily; do not take more than 2 teaspoonfuls (tsp) in 24 hours
children 2 to under 6 years of age | 1 teaspoonful (tsp) daily; do not take more than 1 teaspoonful (tsp) in 24 hours
children under 2 years of age | ask a doctor
consumers with liver or kidney disease | ask a doctor

Other information

- do not use if carton is opened, or if printed neckband is broken or missing
- store between 20° to 25°C (68° to 77°F)

Inactive ingredients

edetate disodium, glycerin, maltitol, monobasic sodium phosphate, natural and artificial grape flavor, phosphoric acid, propylene glycol, purified water, sodium benzoate, sorbitol, sucralose

Questions or comments?

To report SUSPECTED ADVERSE REACTIONS, contact the FDA at 1-800-FDA-1088 or https://www.fda.gov/medwatch/report.htm

DISTRIBUTED BY:

ATLANTIC BIOLOGICALS

MIAMI,FL 33179

Package/Label Principal Display Panel

Compare to the active ingredient in Children’s Claritin®

children’s loratadine oral solution

loratadine oral solution USP, 5 mg/5 mL

antihistamine

allergy

indoor & outdoor allergies

non-drowsy*

24-hour relief of:

• sneezing

• runny nose

• itchy, watery eyes

• itchy throat or nose

dye-free

sugar-free

ages 2 years and older

*when taken as directed. See drug facts panel.

grape flavor